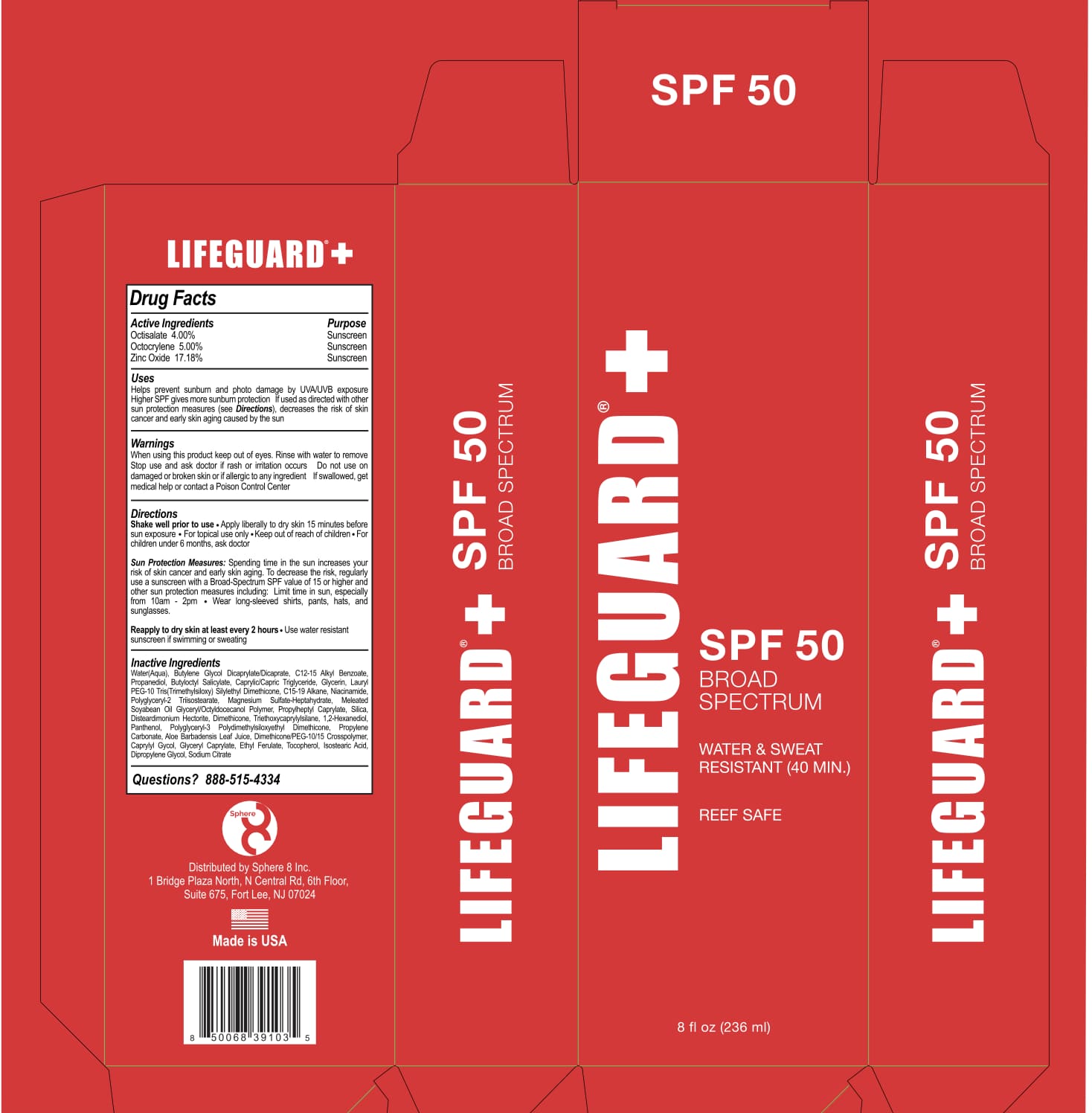 DRUG LABEL: Lifeguard
NDC: 85527-111 | Form: CREAM
Manufacturer: SPHERE 8 INC
Category: otc | Type: HUMAN OTC DRUG LABEL
Date: 20250428

ACTIVE INGREDIENTS: OCTISALATE 4 g/100 mL; ZINC OXIDE 17.18 g/100 mL; OCTOCRYLENE 5 g/100 mL
INACTIVE INGREDIENTS: ETHYL FERULATE; TOCOPHEROL; GLYCERIN; ALKYL (C12-15) BENZOATE; ISOSTEARIC ACID; MAGNESIUM SULFATE HEPTAHYDRATE; POLYGLYCERYL-3 POLYDIMETHYLSILOXYETHYL DIMETHICONE (4000 MPA.S); SOYBEAN OIL; PROPYLHEPTYL CAPRYLATE; DIMETHICONE; ISODODECANE; WATER; BUTYLENE GLYCOL DICAPRYLATE/DICAPRATE; PROPANEDIOL; BUTYLOCTYL SALICYLATE; CAPRYLIC/CAPRIC TRIGLYCERIDE; C15-19 ALKANE; NIACINAMIDE; 1,2-HEXANEDIOL; PANTHENOL; PROPYLENE CARBONATE; CAPRYLYL GLYCOL; GLYCERYL CAPRYLATE; DIPROPYLENE GLYCOL; ALOE VERA LEAF JUICE; CETYL DIGLYCERYL TRIS(TRIMETHYLSILOXY)SILYLETHYL DIMETHICONE (3500 MM2/S); POLYGLYCERYL-2 TRIISOSTEARATE; SILICA; DISTEARDIMONIUM HECTORITE; TRIETHOXYCAPRYLYLSILANE; DIMETHICONE/PEG-10/15 CROSSPOLYMER; SODIUM CITRATE

SPHERE 8- Sunscreen 50 SPF

Active Ingredient(s)

Octisalate 4% Sunscreen

Octocrylene 5% Sunscreen

Zinc Oxide 17.18% Sunscreen

Purpose

Sunscreen

Use

Helps prevent sunburn and photo damage by UV/UVB exposure Higher SPF gives more sunburn protection. If used as directed with other sun protection measures (see Directions), decreases the risk of skin cancer and early skin aging caused by the sun.

Warnings

- When using this product keep out of eyes. Rinse with water to remove Stop use and ask doctor if rash or irritation occurs Do not use on damaged or broken skin or if allergic to any ingredient If swallowed, get medical help or contact a Poison Control Center

WHEN USING

Rinse with water to remove Stop use and ask doctor if rash or irritation occurs

KEEP OUT OF REACH OF CHILDREN

If more than used for brushing is accidentally swallowed, get medical help or contact a Poison Control Center immediately.

Directions

- Shake well prior to use • Apply liberally to dry skin 15 minutes before sun exposure • For topical use only .Keep out of reach of children. For children under 6 months, ask doctor

- Sun Protection Measures: Spending time in the sun increases your risk of skin cancer and early skin aging. To decrease the nsk, regularly use a suns een with a Broad-Spectrum SPF value of 15 or higher and other sun protection measures including: Limit bane in sun, especially from 10am - 2pm

- Wear long-sleeved stilts, pants, hats, and sunglasses, Reapply to dry skin at least every 2 hours. Use water resistant sunscreen if swimming or sweating.

Other information

Protect from excessive heat.

Inactive ingredients

Water(Aqua), Boyle* Glycol DicaorylateXicarxete, C12-15 Alkyl Benzoate, Propanedi01, Elutyloctyi Salicylat, CvryliciCapric Triglyteride, Glycerin, Lally PEG-10 Tris(Trimethylsilm) ilyiettyil Dimethiccne, C15-19 Mane, Niaciriamide, Polyglycenii-2 Triisosbearate, Magnesium Stitata-Heolatrydraie, Meleafied Soy can Oil GlycenflOctyklooecanol Polymer, Propylheptyl Caprylata, Silica, Dlabserdirnohlurn Hed01149, Dirnerlipme, Triethoxycaorytylsilane, 1,2-Hexanaciol, Pentlienol, Polyglycerk3 PolydlmeNsfoxyethyl Dinethicone, Propylene Carbonate, Aloe Berbadensis Leaf Juice, DirnethiconelPEG-1015 Crosspolymer, Cactityl Gycol, Glycerii Capritare, Ethyl Ferulate, Tocopherol, tsostearic Acid, Dipropylene Gird, Sodium Citrate